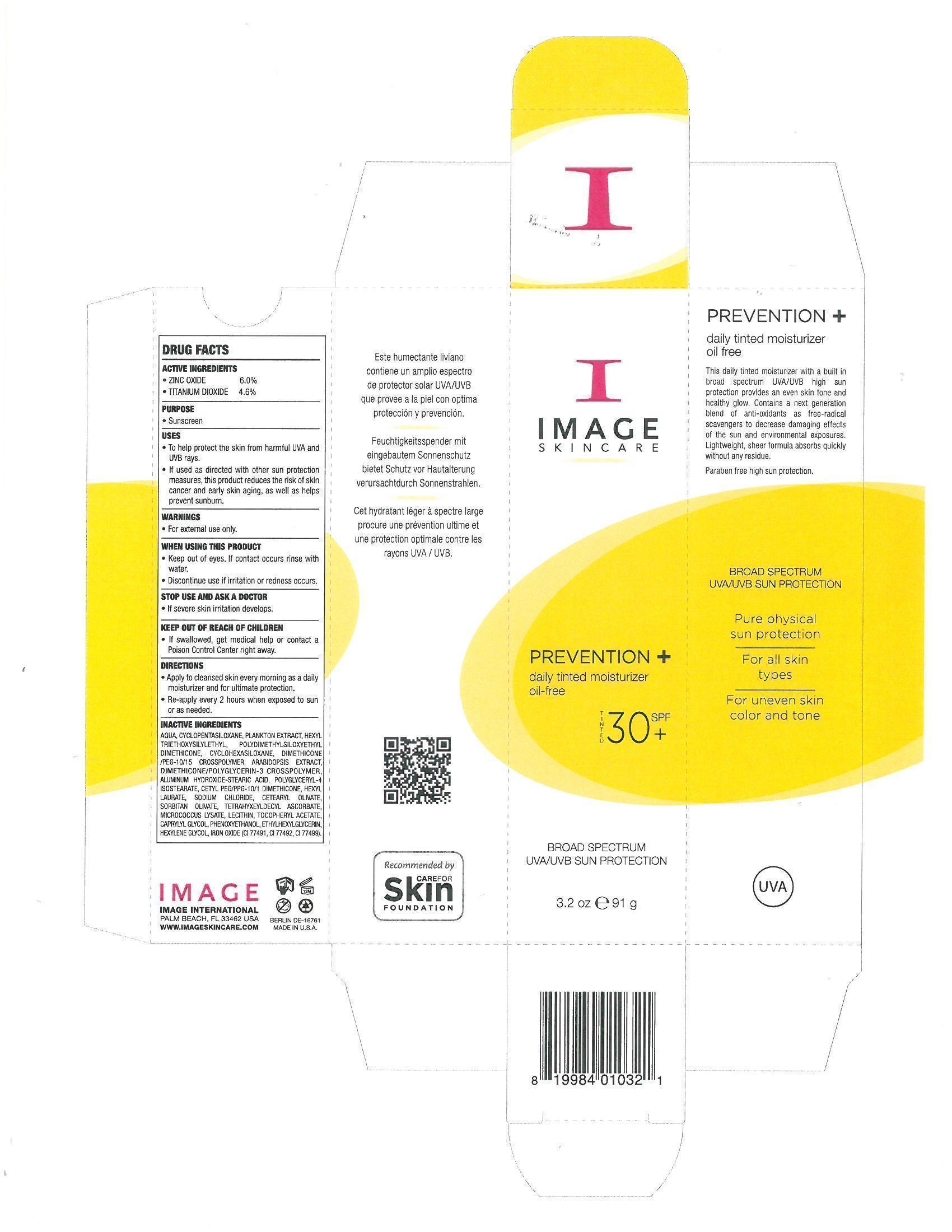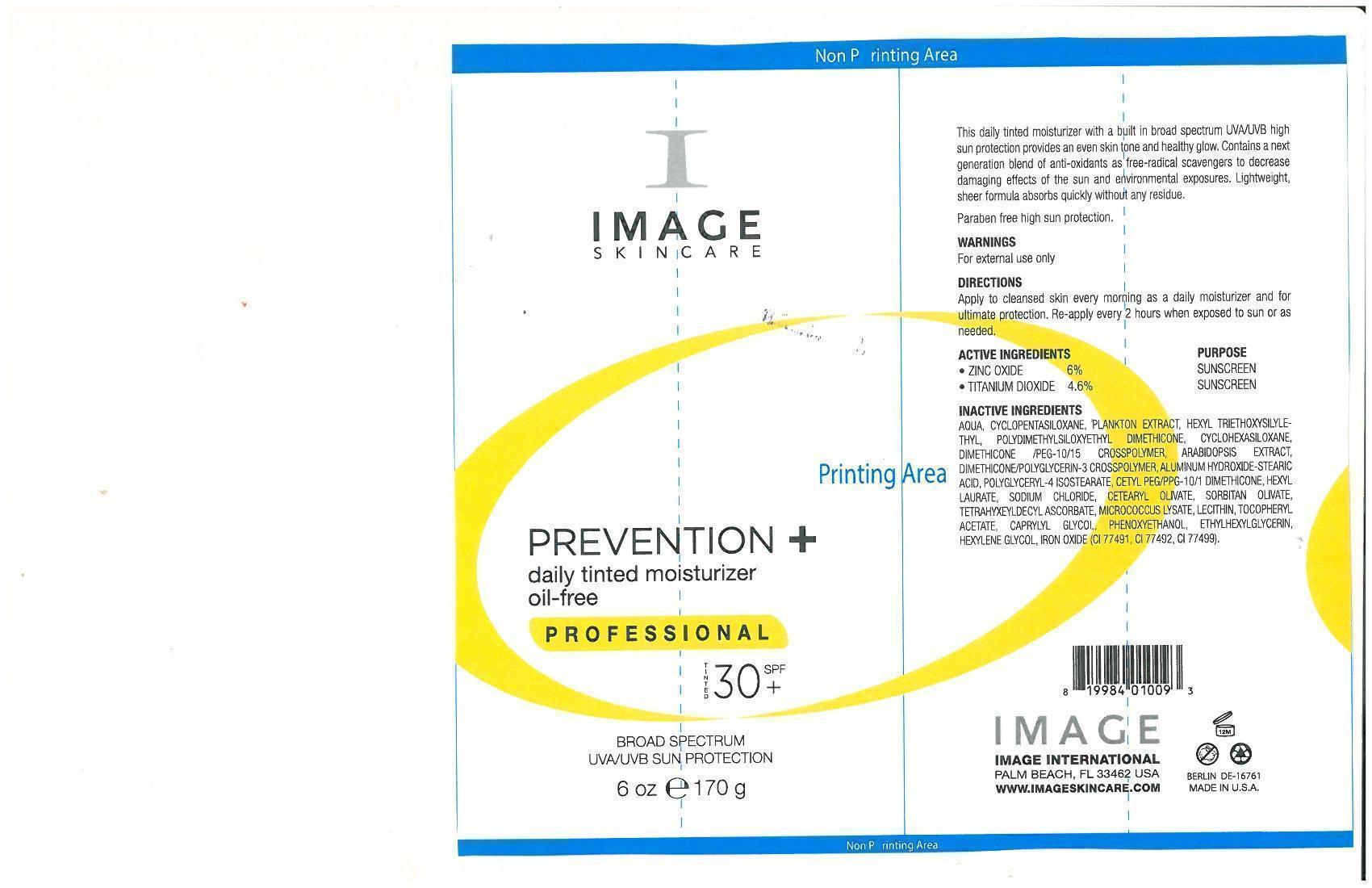 DRUG LABEL: Prevention  daily tinted mositurizer oil-free Tinted 30
NDC: 62742-4067 | Form: CREAM
Manufacturer: Allure Labs, Inc
Category: otc | Type: HUMAN OTC DRUG LABEL
Date: 20140509

ACTIVE INGREDIENTS: ZINC OXIDE 60 mg/1 g; TITANIUM DIOXIDE 46 mg/1 g
INACTIVE INGREDIENTS: WATER; CYCLOMETHICONE 6; ARABIDOPSIS THALIANA; ALUMINUM HYDROXIDE; STEARIC ACID; POLYGLYCERYL-4 ISOSTEARATE; CETYL PEG/PPG-10/1 DIMETHICONE (HLB 4); HEXYL LAURATE; SODIUM CHLORIDE; CETEARYL OLIVATE; SORBITAN OLIVATE; TETRAHEXYLDECYL ASCORBATE; EGG PHOSPHOLIPIDS; .ALPHA.-TOCOPHEROL ACETATE; CAPRYLYL GLYCOL; PHENOXYETHANOL ; ETHYLHEXYLGLYCERIN; HEXYLENE GLYCOL; FERRIC OXIDE RED ; FERRIC OXIDE YELLOW

DRUG FACTS

ACTIVE INGREDIENTS:
Zinc Oxide - 6.0%
Titanium Dioxide 4.6%

Purpose: Sunscreen

Uses:

- To help protect the skin from harmful UVA and UVB rays.
- If used as directed with other sun protection measures, this product reduces the risk of skin cancer and early skin aging, as well as helps prevent sunburn.

Warnings

For External Use Only

WHEN USING

- Keep out of eyes. If contact occurs rinse with water.

- Discontinue use of irritation or redness occurs

STOP USE

if severe skin irritation develops

KEEP OUT OF REACH OF CHILDREN

if swallowed, get medical help or contact a Poison Control Center right away

Directions

- Apply to cleansed skin every morning as daily moisturizer and for ultimate protection
- Re-apply every 2 hours when exposed to sun or as needed

INACTIVE INGREDIENT

Aqua, Cyclopentasiloxane, Plankton Extract, Hexyl Triethoxysilylethyl, Polydimethylsiloxyethyl Dimethicone, Cyclohexasiloxane, Dimethicone/PEG-10/15 Crosspolymer, Arabidopsis Extract, Dimethicone/Polyglycerin -3 Crosspolymer, Aluminum Hydroxide Stearic Acid, Polyglyceryl-4 Isostearate, Cetyl PEG/PPG-10/1 Dimethicone, Hexyl Laurate, Sodium Chloride, Cetearyl Olivate, Tetrahexyldecyl Ascorbate, Micrococcus Lysate, Lecithin, Tocopheryl Acetate, Caprylyl Glycol, Phenoxyethanol, Ethylhexylglycerin, Hexylene Glycol, Iron Oxide (CI77491, CI77492, CI77499)

PACKAGE LABEL

Image International Palm Beach, FL 33462 USA www.imageskincare.com